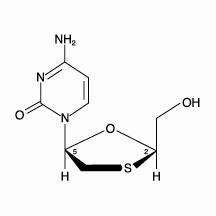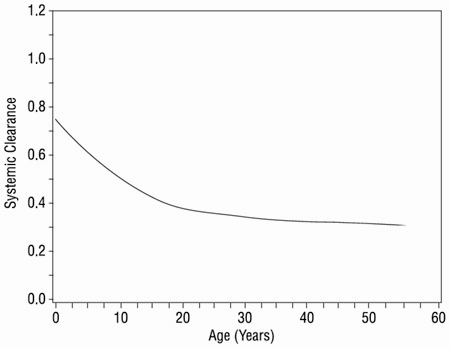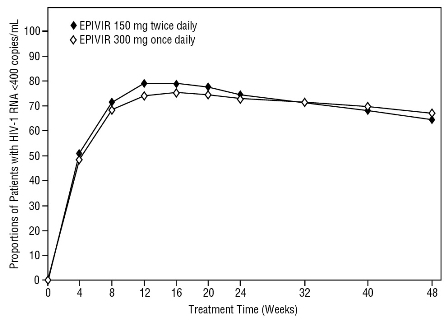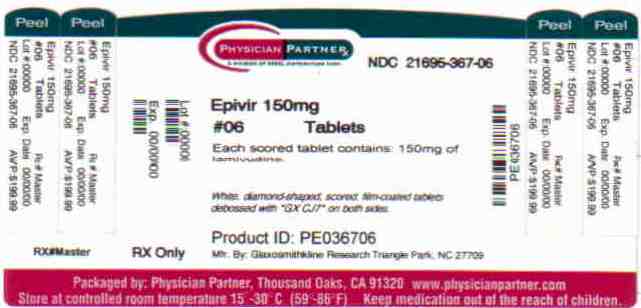 DRUG LABEL: EPIVIR
NDC: 21695-367 | Form: TABLET, FILM COATED
Manufacturer: Rebel Distributors Corp
Category: prescription | Type: HUMAN PRESCRIPTION DRUG LABEL
Date: 20100924

ACTIVE INGREDIENTS: LAMIVUDINE 150 mg/1 1
INACTIVE INGREDIENTS: HYPROMELLOSES; MAGNESIUM STEARATE; CELLULOSE, MICROCRYSTALLINE; POLYETHYLENE GLYCOL; POLYSORBATE 80; SODIUM STARCH GLYCOLATE TYPE A POTATO; TITANIUM DIOXIDE

HIGHLIGHTS OF PRESCRIBING INFORMATION

These highlights do not include all the information needed to use EPIVIR safely and effectively. See full prescribing information for EPIVIR.
EPIVIR (lamivudine) Tablets and Oral Solution
Initial U.S. Approval: 1995

RECENT MAJOR CHANGES

Dosage and Administration, Pediatric Patients (2.2) February 2008

WARNING: RISK OF LACTIC ACIDOSIS, EXACERBATIONS OF HEPATITIS B IN CO-INFECTED PATIENTS UPON DISCONTINUATION OF EPIVIR , DIFFERENT FORMULATIONS OF EPIVIR.

WARNING: LACTIC ACIDOSIS, POSTTREATMENT EXACERBATIONS OF HEPATITIS B IN CO-INFECTED PATIENTS, DIFFERENT FORMULATIONS OF EPIVIR

See full prescribing information for complete boxed warning

- Lactic acidosis and severe hepatomegaly with steatosis, including fatal cases, have been reported with the use of nucleoside analogues. Suspend treatment if clinical or laboratory findings suggestive of lactic acidosis or pronounced hepatotoxicity occur. (5.1)
- Severe acute exacerbations of hepatitis B have been reported in patients who are co-infected with hepatitis B virus (HBV) and human immunodeficiency virus (HIV-1) and have discontinued EPIVIR. Monitor hepatic function closely in these patients and, if appropriate, initiate anti-hepatitis B treatment. (5.2)
- Patients with HIV-1 infection should receive only dosage forms of EPIVIR appropriate for treatment of HIV-1. (5.2)

1 INDICATIONS AND USAGE

EPIVIR is a nucleoside analogue reverse transcriptase inhibitor indicated in combination with other antiretroviral agents for the treatment of HIV-1 infection. Limitation of Use: The dosage of this product is for HIV-1 and not for HBV. (1)

2 DOSAGE AND ADMINISTRATION

- Adults and adolescents >16 years of age: 300 mg daily, administered as either 150 mg twice daily or 300 mg once daily. (2.1)
- Pediatric patients 3 months up to 16 years of age: Dosage should be based on body weight. (2.2)
- Patients With Renal Impairment: Doses of EPIVIR must be adjusted in accordance with renal function. (2.3)

3 DOSAGE FORMS AND STRENGTHS

- Tablets: 300 mg (3)
- Tablets: Scored 150 mg (3)
- Oral Solution: 10 mg/mL (3)

4 CONTRAINDICATIONS

EPIVIR Tablets and Oral Solution are contraindicated in patients with previously demonstrated clinically significant hypersensitivity (e.g., anaphylaxis) to any of the components of the products. (4)

5 WARNINGS AND PRECAUTIONS

- Lactic acidosis and severe hepatomegaly with steatosis: Reported with the use of nucleoside analogues. Suspend treatment if clinical or laboratory findings suggestive of lactic acidosis or pronounced hepatoxicity occur. (5.1)
- Severe acute exacerbations of hepatitis: Reported in patients who are co-infected with hepatitis B virus and HIV-1 and discontinued EPIVIR. Monitor hepatic function closely in these patients and, if appropriate, initiate anti-hepatitis B treatment. (5.2)
- Patients with HIV-1 infection should receive only dosage forms of EPIVIR appropriate for treatment of HIV-1. (5.2)
- Co-infected HIV-1/HBV Patients: Emergence of lamivudine-resistant HBV variants associated with lamivudine-containing antiretroviral regimens has been reported. (5.2)
- Emtricitabine should not be administered concomitantly with lamivudine-containing products. (5.3)
- Hepatic decompensation (some fatal) has occurred in HIV-1/HCV co-infected patients receiving interferon and ribavirin-based regimens. Monitor for treatment-associated toxicities. Discontinue EPIVIR as medically appropriate and consider dose reduction or discontinuation of interferon alfa, ribavirin, or both. (5.4)
- Pancreatitis: Use with caution in pediatric patients with a history of pancreatitis or other significant risk factors for pancreatitis. Discontinue treatment as clinically appropriate. (5.5)
- Immune reconstitution syndrome (5.6) and redistribution/accumulation of body fat (5.7) have been reported in patients treated with combination antiretroviral therapy.

6 ADVERSE REACTIONS

- The most common reported adverse reactions (incidence ≥15%) in adults were headache, nausea, malaise and fatigue, nasal signs and symptoms, diarrhea, and cough. (6.1)
- The most common reported adverse reactions (incidence ≥15%) in pediatric patients were fever and cough. (6.1)
  To report SUSPECTED ADVERSE REACTIONS, contact GlaxoSmithKline at 1-888-825-5249 or FDA at 1-800-FDA-1088 or www.fda.gov/medwatch.

7 DRUG INTERACTIONS

Zalcitabine is not recommended for use in combination with EPIVIR. (7.2)

8 USE IN SPECIFIC POPULATIONS

- Pregnancy: Physicians are encouraged to register patients in the Antiretroviral Pregnancy Registry by calling 1-800-258-4263. (8.1)

Revised: April 2009
EPV:2PI

FULL PRESCRIBING INFORMATION

WARNING: RISK OF LACTIC ACIDOSIS, EXACERBATIONS OF HEPATITIS B IN CO-INFECTED PATIENTS UPON DISCONTINUATION OF EPIVIR , DIFFERENT FORMULATIONS OF EPIVIR.

Lactic acidosis and severe hepatomegaly with steatosis, including fatal cases, have been reported with the use of nucleoside analogues alone or in combination, including lamivudine and other antiretrovirals. Suspend treatment if clinical or laboratory findings suggestive of lactic acidosis or pronounced hepatotoxicity occur [see Warnings and Precautions (5.1)].

Severe acute exacerbations of hepatitis B have been reported in patients who are co-infected with hepatitis B virus (HBV) and human immunodeficiency virus (HIV-1) and have discontinued EPIVIR. Hepatic function should be monitored closely with both clinical and laboratory follow-up for at least several months in patients who discontinue EPIVIR and are co-infected with HIV-1 and HBV. If appropriate, initiation of anti-hepatitis B therapy may be warranted [see Warnings and Precautions (5.2)].

EPIVIR Tablets and Oral Solution (used to treat HIV-1 infection) contain a higher dose of the active ingredient (lamivudine) than EPIVIR-HBV® Tablets and Oral Solution (used to treat chronic HBV infection). Patients with HIV-1 infection should receive only dosage forms appropriate for treatment of HIV-1 [see Warnings and Precautions (5.2)].

1 INDICATIONS AND USAGE

EPIVIR is a nucleoside analogue indicated in combination with other antiretroviral agents for the treatment of human immunodeficiency virus (HIV-1) infection. Limitation of use: The dosage of this product is for HIV-1 and not for HBV.

2 DOSAGE AND ADMINISTRATION

2.1 Adults and Adolescents >16 years of age

The recommended oral dose of EPIVIR in HIV-1-infected adults and adolescents >16 years of age is 300 mg daily, administered as either 150 mg twice daily or 300 mg once daily, in combination with other antiretroviral agents. If lamivudine is administered to a patient infected with HIV-1 and HBV, the dosage indicated for HIV-1 therapy should be used as part of an appropriate combination regimen [see Warnings and Precautions (5.2)].

2.2 Pediatric Patients

The recommended oral dose of EPIVIR Oral Solution in HIV-1-infected pediatric patients 3 months to 16 years of age is 4 mg/kg twice daily (up to a maximum of 150 mg twice a day), administered in combination with other antiretroviral agents.

EPIVIR is also available as a scored tablet for HIV-1-infected pediatric patients who weigh ≥14 kg and for whom a solid dosage form is appropriate. Before prescribing EPIVIR Tablets, children should be assessed for the ability to swallow tablets. If a child is unable to reliably swallow EPIVIR Tablets, the oral solution formulation should be prescribed. The recommended oral dosage of EPIVIR Tablets for HIV-1-infected pediatric patients is presented in Table 1.

Table 1. Dosing Recommendations for EPIVIR Tablets in Pediatric Patients
Weight; (kg) | Dosage Regimen Using Scored 150-mg Tablet |  | Total Daily Dose
Weight; (kg) | AM Dose | PM Dose | Total Daily Dose
14 to 21 | ½ tablet (75 mg) | ½ tablet (75 mg) | 150 mg
>21 to <30 | ½ tablet (75 mg) | 1 tablet (150 mg) | 225 mg
≥30 | 1 tablet (150 mg) | 1 tablet (150 mg) | 300 mg

2.3 Patients With Renal Impairment

Dosing of EPIVIR is adjusted in accordance with renal function. Dosage adjustments are listed in Table 2 [see Clinical Pharmacology (12.3)].

Table 2. Adjustment of Dosage of EPIVIR in Adults and Adolescents (≥30 kg) in Accordance With Creatinine Clearance
Creatinine Clearance (mL/min) | Recommended Dosage of EPIVIR
≥50 | 150 mg twice daily or 300 mg once daily
30-49 | 150 mg once daily
15-29 | 150 mg first dose, then 100 mg once daily
5-14 | 150 mg first dose, then 50 mg once daily
<5 | 50 mg first dose, then 25 mg once daily

No additional dosing of EPIVIR is required after routine (4-hour) hemodialysis or peritoneal dialysis.

Although there are insufficient data to recommend a specific dose adjustment of EPIVIR in pediatric patients with renal impairment, a reduction in the dose and/or an increase in the dosing interval should be considered.

3 DOSAGE FORMS AND STRENGTHS

- EPIVIR Scored Tablets
  150 mg, are white, diamond-shaped, scored, film-coated tablets debossed with “GX CJ7” on both sides.
- EPIVIR Tablets
  300 mg, are gray, modified diamond-shaped, film-coated tablets engraved with “GX EJ7” on one side and plain on the reverse side.
- EPIVIR Oral Solution
  A clear, colorless to pale yellow, strawberry-banana flavored liquid, containing 10 mg of lamivudine per 1 mL.

4 CONTRAINDICATIONS

EPIVIR Tablets and Oral Solution are contraindicated in patients with previously demonstrated clinically significant hypersensitivity (e.g., anaphylaxis) to any of the components of the products.

5 WARNINGS AND PRECAUTIONS

5.1 Lactic Acidosis/Severe Hepatomegaly With Steatosis

Lactic acidosis and severe hepatomegaly with steatosis, including fatal cases, have been reported with the use of nucleoside analogues alone or in combination, including lamivudine and other antiretrovirals. A majority of these cases have been in women. Obesity and prolonged nucleoside exposure may be risk factors. Particular caution should be exercised when administering EPIVIR to any patient with known risk factors for liver disease; however, cases also have been reported in patients with no known risk factors. Treatment with EPIVIR should be suspended in any patient who develops clinical or laboratory findings suggestive of lactic acidosis or pronounced hepatotoxicity (which may include hepatomegaly and steatosis even in the absence of marked transaminase elevations).

5.2 Patients With HIV-1 and Hepatitis B Virus Co-infection

Posttreatment Exacerbations of Hepatitis: In clinical trials in non-HIV-1-infected patients treated with lamivudine for chronic hepatitis B, clinical and laboratory evidence of exacerbations of hepatitis have occurred after discontinuation of lamivudine. These exacerbations have been detected primarily by serum ALT elevations in addition to re-emergence of HBV DNA. Although most events appear to have been self-limited, fatalities have been reported in some cases. Similar events have been reported from postmarketing experience after changes from lamivudine-containing HIV-1 treatment regimens to non-lamivudine-containing regimens in patients infected with both HIV-1 and HBV. The causal relationship to discontinuation of lamivudine treatment is unknown. Patients should be closely monitored with both clinical and laboratory follow-up for at least several months after stopping treatment. There is insufficient evidence to determine whether re-initiation of lamivudine alters the course of posttreatment exacerbations of hepatitis.

Important Differences Among Lamivudine-Containing Products: EPIVIR Tablets and Oral Solution contain a higher dose of the same active ingredient (lamivudine) than EPIVIR-HBV Tablets and EPIVIR-HBV Oral Solution. EPIVIR-HBV was developed for patients with chronic hepatitis B. The formulation and dosage of lamivudine in EPIVIR-HBV are not appropriate for patients co-infected with HIV-1 and HBV. Safety and efficacy of lamivudine have not been established for treatment of chronic hepatitis B in patients co-infected with HIV-1 and HBV. If treatment with EPIVIR-HBV is prescribed for chronic hepatitis B for a patient with unrecognized or untreated HIV-1 infection, rapid emergence of HIV-1 resistance is likely to result because of the subtherapeutic dose and the inappropriateness of monotherapy HIV-1 treatment. If a decision is made to administer lamivudine to patients co-infected with HIV-1 and HBV, EPIVIR Tablets, EPIVIR Oral Solution, COMBIVIR® (lamivudine/zidovudine) Tablets, EPZICOM® (abacavir sulfate and lamivudine) Tablets, or TRIZIVIR® (abacavir sulfate, lamivudine, and zidovudine) Tablets should be used as part of an appropriate combination regimen.

Emergence of Lamivudine-Resistant HBV: In non–HIV-1-infected patients treated with lamivudine for chronic hepatitis B, emergence of lamivudine-resistant HBV has been detected and has been associated with diminished treatment response (see full prescribing information for EPIVIR-HBV for additional information). Emergence of hepatitis B virus variants associated with resistance to lamivudine has also been reported in HIV-1-infected patients who have received lamivudine-containing antiretroviral regimens in the presence of concurrent infection with hepatitis B virus.

5.3 Use With Other Lamivudine- and Emtricitabine-Containing Products

EPIVIR should not be administered concomitantly with other lamivudine-containing products including EPIVIR-HBV Tablets, EPIVIR Oral Solution, COMBIVIR (lamivudine/zidovudine) Tablets, EPZICOM (abacavir sulfate and lamivudine) Tablets, or TRIZIVIR (abacavir sulfate, lamivudine, and zidovudine) or emtricitabine-containing products, including ATRIPLA® (efavirenz, emtricitabine, and tenofovir), EMTRIVA® (emtricitabine), or TRUVADA® (emtricitabine and tenofovir).

5.4 Use With Interferon- and Ribavirin-Based Regimens

In vitro studies have shown ribavirin can reduce the phosphorylation of pyrimidine nucleoside analogues such as lamivudine. Although no evidence of a pharmacokinetic or pharmacodynamic interaction (e.g., loss of HIV-1/HCV virologic suppression) was seen when ribavirin was coadministered with lamivudine in HIV-1/HCV co-infected patients [see Clinical Pharmacology (12.3)], hepatic decompensation (some fatal) has occurred in HIV-1/HCV co-infected patients receiving combination antiretroviral therapy for HIV-1 and interferon alfa with or without ribavirin. Patients receiving interferon alfa with or without ribavirin and EPIVIR should be closely monitored for treatment-associated toxicities, especially hepatic decompensation. Discontinuation of EPIVIR should be considered as medically appropriate. Dose reduction or discontinuation of interferon alfa, ribavirin, or both should also be considered if worsening clinical toxicities are observed, including hepatic decompensation (e.g., Child-Pugh >6). See the complete prescribing information for interferon and ribavirin.

5.5 Pancreatitis

In pediatric patients with a history of prior antiretroviral nucleoside exposure, a history of pancreatitis, or other significant risk factors for the development of pancreatitis, EPIVIR should be used with caution. Treatment with EPIVIR should be stopped immediately if clinical signs, symptoms, or laboratory abnormalities suggestive of pancreatitis occur [see Adverse Reactions (6.1)].

5.6 Immune Reconstitution Syndrome

Immune reconstitution syndrome has been reported in patients treated with combination antiretroviral therapy, including EPIVIR. During the initial phase of combination antiretroviral treatment, patients whose immune system responds may develop an inflammatory response to indolent or residual opportunistic infections (such as Mycobacterium avium infection, cytomegalovirus, Pneumocystis jirovecii pneumonia [PCP], or tuberculosis), which may necessitate further evaluation and treatment.

5.7 Fat Redistribution

Redistribution/accumulation of body fat including central obesity, dorsocervical fat enlargement (buffalo hump), peripheral wasting, facial wasting, breast enlargement, and “cushingoid appearance” have been observed in patients receiving antiretroviral therapy. The mechanism and long-term consequences of these events are currently unknown. A causal relationship has not been established.

6 ADVERSE REACTIONS

6.1 Clinical Trials Experience

The following adverse reactions are discussed in greater detail in other sections of the labeling:

- Lactic acidosis and severe hepatomegaly with steatosis [see Boxed Warning, Warnings and Precautions (5.1)].
- Severe acute exacerbations of hepatitis B [see Boxed Warning, Warnings and Precautions (5.2)].
- Hepatic decompensation in patients co-infected with HIV-1 and Hepatitis C [see Warnings and Precautions (5.4)].
- Pancreatitis [see Warnings and Precautions (5.5)].

Because clinical trials are conducted under widely varying conditions, adverse reaction rates observed in the clinical trials of a drug cannot be directly compared to rates in the clinical trials of another drug and may not reflect the rates observed in practice.

Adults - Clinical Trials in HIV-1: The safety profile of EPIVIR in adults is primarily based on 3,568 HIV-1-infected patients in 7 clinical trials.

The most common adverse reactions are headache, nausea, malaise, fatigue, nasal signs and symptoms, diarrhea and cough.

Selected clinical adverse reactions in ≥5% of patients during therapy with EPIVIR 150 mg twice daily plus RETROVIR® 200 mg 3 times daily for up to 24 weeks are listed in Table 3.

Table 3. Selected Clinical Adverse Reactions (≥5% Frequency) in Four Controlled Clinical Trials (NUCA3001, NUCA3002, NUCB3001, NUCB3002)
Adverse Reaction | EPIVIR 150 mg Twice Daily plus RETROVIR; (n = 251) | RETROVIRa; (n = 230)
Body as a Whole
Headache | 35% | 27%
Malaise & fatigue | 27% | 23%
Fever or chills | 10% | 12%
Digestive
Nausea | 33% | 29%
Diarrhea | 18% | 22%
Nausea & vomiting | 13% | 12%
Anorexia and/or decreased appetite | 10% | 7%
Abdominal pain | 9% | 11%
Abdominal cramps | 6% | 3%
Dyspepsia | 5% | 5%
Nervous System
Neuropathy | 12% | 10%
Insomnia & other sleep disorders | 11% | 7%
Dizziness | 10% | 4%
Depressive disorders | 9% | 4%
Respiratory
Nasal signs & symptoms | 20% | 11%
Cough | 18% | 13%
Skin
Skin rashes | 9% | 6%
Musculoskeletal
Musculoskeletal pain | 12% | 10%
Myalgia | 8% | 6%
Arthralgia | 5% | 5%
a Either zidovudine monotherapy or zidovudine in combination with zalcitabine.

Pancreatitis: Pancreatitis was observed in 9 out of 2,613 adult patients (0.3%) who received EPIVIR in controlled clinical trials EPV20001, NUCA3001, NUCB3001, NUCA3002, NUCB3002, and NUCB3007 [see Warnings and Precautions (5.5)].

EPIVIR 300 mg Once Daily: The types and frequencies of clinical adverse reactions reported in patients receiving EPIVIR 300 mg once daily or EPIVIR 150 mg twice daily (in 3-drug combination regimens in EPV20001 and EPV40001) for 48 weeks were similar.

Selected laboratory abnormalities observed during therapy are summarized in Table 4.

Table 4. Frequencies of Selected Grade 3-4 Laboratory Abnormalities in Adults in Four 24-Week Surrogate Endpoint Studies (NUCA3001, NUCA3002, NUCB3001, NUCB3002) and a Clinical Endpoint Study (NUCB3007)
Test; (Threshold Level) | 24-Week Surrogate Endpoint; Studiesa |  | Clinical Endpoint; Studya
Test; (Threshold Level) | EPIVIR plus; RETROVIR | RETROVIRb | EPIVIR plus; Current Therapy | Placebo plus; Current Therapyc
Absolute neutrophil count (<750/mm^3) | 7.2% | 5.4% | 15% | 13%
Hemoglobin (<8.0 g/dL) | 2.9% | 1.8% | 2.2% | 3.4%
Platelets (<50,000/mm^3) | 0.4% | 1.3% | 2.8% | 3.8%
ALT (>5.0 x ULN) | 3.7% | 3.6% | 3.8% | 1.9%
AST (>5.0 x ULN) | 1.7% | 1.8% | 4.0% | 2.1%
Bilirubin (>2.5 x ULN) | 0.8% | 0.4% | ND | ND
Amylase (>2.0 x ULN) | 4.2% | 1.5% | 2.2% | 1.1%
a The median duration on study was 12 months.
b Either zidovudine monotherapy or zidovudine in combination with zalcitabine.
c Current therapy was either zidovudine, zidovudine plus didanosine, or zidovudine plus zalcitabine.
ULN = Upper limit of normal.
ND = Not done.

The frequencies of selected laboratory abnormalities reported in patients receiving EPIVIR 300 mg once daily or EPIVIR 150 mg twice daily (in 3-drug combination regimens in EPV20001 and EPV40001) were similar.

Pediatric Patients – Clinical Trials in HIV-1: EPIVIR Oral Solution has been studied in 638 pediatric patients 3 months to 18 years of age in 3 clinical trials.

Selected clinical adverse reactions and physical findings with a ≥5% frequency during therapy with EPIVIR 4 mg/kg twice daily plus RETROVIR 160 mg/m^2 3 times daily in therapy-naive (≤56 days of antiretroviral therapy) pediatric patients are listed in Table 5.

Table 5. Selected Clinical Adverse Reactions and Physical Findings (≥5% Frequency) in Pediatric Patients in Study ACTG300
Adverse Reaction | EPIVIR plus; RETROVIR; (n = 236) | Didanosine; (n = 235)
Body as a Whole
Fever | 25% | 32%
Digestive
Hepatomegaly | 11% | 11%
Nausea & vomiting | 8% | 7%
Diarrhea | 8% | 6%
Stomatitis | 6% | 12%
Splenomegaly | 5% | 8%
Respiratory
Cough | 15% | 18%
Abnormal breath sounds/wheezing | 7% | 9%
Ear, Nose, and Throat
Signs or symptoms of earsa | 7% | 6%
Nasal discharge or congestion | 8% | 11%
Other
Skin rashes | 12% | 14%
Lymphadenopathy | 9% | 11%
a Includes pain, discharge, erythema, or swelling of an ear.

Pancreatitis: Pancreatitis, which has been fatal in some cases, has been observed in antiretroviral nucleoside-experienced pediatric patients receiving EPIVIR alone or in combination with other antiretroviral agents. In an open-label dose-escalation study (NUCA2002), 14 patients (14%) developed pancreatitis while receiving monotherapy with EPIVIR. Three of these patients died of complications of pancreatitis. In a second open-label study (NUCA2005), 12 patients (18%) developed pancreatitis. In Study ACTG300, pancreatitis was not observed in 236 patients randomized to EPIVIR plus RETROVIR. Pancreatitis was observed in 1 patient in this study who received open-label EPIVIR in combination with RETROVIR and ritonavir following discontinuation of didanosine monotherapy [see Warnings and Precautions (5.5)].

Paresthesias and Peripheral Neuropathies: Paresthesias and peripheral neuropathies were reported in 15 patients (15%) in Study NUCA2002, 6 patients (9%) in Study NUCA2005, and 2 patients (<1%) in Study ACTG300.

Selected laboratory abnormalities experienced by therapy-naive (≤56 days of antiretroviral therapy) pediatric patients are listed in Table 6.

Table 6. Frequencies of Selected Grade 3-4 Laboratory Abnormalities in Pediatric Patients in Study ACTG300
Test; (Threshold Level) | EPIVIR plus; RETROVIR | Didanosine
Absolute neutrophil count (<400/mm^3) | 8% | 3%
Hemoglobin (<7.0 g/dL) | 4% | 2%
Platelets (<50,000/mm^3) | 1% | 3%
ALT (>10 x ULN) | 1% | 3%
AST (>10 x ULN) | 2% | 4%
Lipase (>2.5 x ULN) | 3% | 3%
Total Amylase (>2.5 x ULN) | 3% | 3%
ULN = Upper limit of normal.

Neonates - Clinical Trials in HIV-1: Limited short-term safety information is available from 2 small, uncontrolled studies in South Africa in neonates receiving lamivudine with or without zidovudine for the first week of life following maternal treatment starting at Week 38 or 36 of gestation [see Clinical Pharmacology (12.3)]. Selected adverse reactions reported in these neonates included increased liver function tests, anemia, diarrhea, electrolyte disturbances, hypoglycemia, jaundice and hepatomegaly, rash, respiratory infections, and sepsis; 3 neonates died (1 from gastroenteritis with acidosis and convulsions, 1 from traumatic injury, and 1 from unknown causes). Two other nonfatal gastroenteritis or diarrhea cases were reported, including 1 with convulsions; 1 infant had transient renal insufficiency associated with dehydration. The absence of control groups limits assessments of causality, but it should be assumed that perinatally exposed infants may be at risk for adverse reactions comparable to those reported in pediatric and adult HIV-1-infected patients treated with lamivudine-containing combination regimens. Long-term effects of in utero and infant lamivudine exposure are not known.

6.2 Postmarketing Experience

In addition to adverse reactions reported from clinical trials, the following adverse reactions have been reported during postmarketing use of EPIVIR. Because these reactions are reported voluntarily from a population of unknown size, estimates of frequency cannot be made. These reactions have been chosen for inclusion due to a combination of their seriousness, frequency of reporting, or potential causal connection to lamivudine.

Body as a Whole: Redistribution/accumulation of body fat [see Warnings and Precautions (5.7)].

Endocrine and Metabolic: Hyperglycemia.

General: Weakness.

Hemic and Lymphatic: Anemia (including pure red cell aplasia and severe anemias progressing on therapy).

Hepatic and Pancreatic: Lactic acidosis and hepatic steatosis, posttreatment exacerbation of hepatitis B [see Boxed Warning, Warnings and Precautions (5.1, 5.2)].

Hypersensitivity: Anaphylaxis, urticaria.

Musculoskeletal: Muscle weakness, CPK elevation, rhabdomyolysis.

Skin: Alopecia, pruritus.

7 DRUG INTERACTIONS

Lamivudine is predominantly eliminated in the urine by active organic cationic secretion. The possibility of interactions with other drugs administered concurrently should be considered, particularly when their main route of elimination is active renal secretion via the organic cationic transport system (e.g., trimethoprim). No data are available regarding interactions with other drugs that have renal clearance mechanisms similar to that of lamivudine.

7.1 Interferon- and Ribavirin-Based Regimens

Although no evidence of a pharmacokinetic or pharmacodynamic interaction (e.g., loss of HIV-1/HCV virologic suppression) was seen when ribavirin was coadministered with lamivudine in HIV-1/HCV co-infected patients, hepatic decompensation (some fatal) has occurred in HIV-1/HCV co-infected patients receiving combination antiretroviral therapy for HIV-1 and interferon alfa with or without ribavirin [see Warnings and Precautions (5.4), Clinical Pharmacology (12.3)].

7.2 Zalcitabine

Lamivudine and zalcitabine may inhibit the intracellular phosphorylation of one another. Therefore, use of lamivudine in combination with zalcitabine is not recommended.

7.3 Trimethoprim/Sulfamethoxazole (TMP/SMX)

No change in dose of either drug is recommended. There is no information regarding the effect on lamivudine pharmacokinetics of higher doses of TMP/SMX such as those used to treat PCP.

7.4 Drugs with No Observed Interactions With EPIVIR

A drug interaction study showed no clinically significant interaction between EPIVIR and zidovudine.

8 USE IN SPECIFIC POPULATIONS

8.1 Pregnancy

Pregnancy Category C. There are no adequate and well-controlled studies of EPIVIR in pregnant women. Animal reproduction studies in rats and rabbits revealed no evidence of teratogenicity. Increased early embryolethality occurred in rabbits at exposure levels similar to those in humans. EPIVIR should be used during pregnancy only if the potential benefit justifies the potential risk to the fetus.

Lamivudine pharmacokinetics were studied in pregnant women during 2 clinical studies conducted in South Africa. The study assessed pharmacokinetics in: 16 women at 36 weeks gestation using 150 mg lamivudine twice daily with zidovudine, 10 women at 38 weeks gestation using 150 mg lamivudine twice daily with zidovudine, and 10 women at 38 weeks gestation using lamivudine 300 mg twice daily without other antiretrovirals. These studies were not designed or powered to provide efficacy information. Lamivudine pharmacokinetics in pregnant women were similar to those seen in non-pregnant adults and in postpartum women. Lamivudine concentrations were generally similar in maternal, neonatal, and umbilical cord serum samples. In a subset of subjects, lamivudine amniotic fluid specimens were collected following natural rupture of membranes. Amniotic fluid concentrations of lamivudine were typically 2 times greater than maternal serum levels and ranged from 1.2 to 2.5 mcg/mL (150 mg twice daily) and 2.1 to 5.2 mcg/mL (300 mg twice daily). It is not known whether risks of adverse events associated with lamivudine are altered in pregnant women compared with other HIV-1-infected patients.

Animal reproduction studies performed at oral doses up to 130 and 60 times the adult dose in rats and rabbits, respectively, revealed no evidence of teratogenicity due to lamivudine. Increased early embryolethality occurred in rabbits at exposure levels similar to those in humans. However, there was no indication of this effect in rats at exposure levels up to 35 times those in humans. Based on animal studies, lamivudine crosses the placenta and is transferred to the fetus [see Nonclinical Toxicology (13.2)].

Antiretroviral Pregnancy Registry: To monitor maternal-fetal outcomes of pregnant women exposed to lamivudine, a Pregnancy Registry has been established. Physicians are encouraged to register patients by calling 1-800-258-4263.

8.3 Nursing Mothers

The Centers for Disease Control and Prevention recommend that HIV-1-infected mothers in the United States not breastfeed their infants to avoid risking postnatal transmission of HIV-1 infection. Because of the potential for serious adverse reactions in nursing infants and HIV-1 transmission, mothers should be instructed not to breastfeed if they are receiving lamivudine.

Lamivudine is excreted into human milk. Samples of breast milk obtained from 20 mothers receiving lamivudine monotherapy (300 mg twice daily) or combination therapy (150 mg lamivudine twice daily and 300 mg zidovudine twice daily) had measurable concentrations of lamivudine.

8.4 Pediatric Use

The safety and effectiveness of twice-daily EPIVIR in combination with other antiretroviral agents have been established in pediatric patients 3 months and older [see Adverse Reactions (6.1), Clinical Pharmacology (12.3), Clinical Studies (14.2)].

8.5 Geriatric Use

Clinical studies of EPIVIR did not include sufficient numbers of subjects aged 65 and over to determine whether they respond differently from younger subjects. In general, dose selection for an elderly patient should be cautious, reflecting the greater frequency of decreased hepatic, renal, or cardiac function, and of concomitant disease or other drug therapy. In particular, because lamivudine is substantially excreted by the kidney and elderly patients are more likely to have decreased renal function, renal function should be monitored and dosage adjustments should be made accordingly [see Dosage and Administration (2.3), Clinical Pharmacology (12.3)].

8.6 Patients With Impaired Renal Function

Reduction of the dosage of EPIVIR is recommended for patients with impaired renal function [see Dosage and Administration (2.3), Clinical Pharmacology (12.3)].

10 OVERDOSAGE

There is no known antidote for EPIVIR. One case of an adult ingesting 6 g of EPIVIR was reported; there were no clinical signs or symptoms noted and hematologic tests remained normal. Two cases of pediatric overdose were reported in Study ACTG300. One case involved a single dose of 7 mg/kg of EPIVIR; the second case involved use of 5 mg/kg of EPIVIR twice daily for 30 days. There were no clinical signs or symptoms noted in either case. Because a negligible amount of lamivudine was removed via (4-hour) hemodialysis, continuous ambulatory peritoneal dialysis, and automated peritoneal dialysis, it is not known if continuous hemodialysis would provide clinical benefit in a lamivudine overdose event. If overdose occurs, the patient should be monitored, and standard supportive treatment applied as required.

11 DESCRIPTION

EPIVIR (also known as 3TC) is a brand name for lamivudine, a synthetic nucleoside analogue with activity against HIV-1 and HBV. The chemical name of lamivudine is (2R,cis)-4-amino-1-(2-hydroxymethyl-1,3-oxathiolan-5-yl)-(1H)-pyrimidin-2-one. Lamivudine is the (-)enantiomer of a dideoxy analogue of cytidine. Lamivudine has also been referred to as (-)2′,3′-dideoxy, 3′-thiacytidine. It has a molecular formula of C8H11N3O3S and a molecular weight of 229.3. It has the following structural formula:

Lamivudine is a white to off-white crystalline solid with a solubility of approximately 70 mg/mL in water at 20°C.

EPIVIR Tablets are for oral administration. Each scored 150-mg film-coated tablet contains 150 mg of lamivudine and the inactive ingredients hypromellose, magnesium stearate, microcrystalline cellulose, polyethylene glycol, polysorbate 80, sodium starch glycolate, and titanium dioxide.

Each 300-mg film-coated tablet contains 300 mg of lamivudine and the inactive ingredients black iron oxide, hypromellose, magnesium stearate, microcrystalline cellulose, polyethylene glycol, polysorbate 80, sodium starch glycolate, and titanium dioxide.

EPIVIR Oral Solution is for oral administration. One milliliter (1 mL) of EPIVIR Oral Solution contains 10 mg of lamivudine (10 mg/mL) in an aqueous solution and the inactive ingredients artificial strawberry and banana flavors, citric acid (anhydrous), methylparaben, propylene glycol, propylparaben, sodium citrate (dihydrate), and sucrose (200 mg).

12 CLINICAL PHARMACOLOGY

12.1 Mechanism of Action

Lamivudine is an antiviral agent [see Clinical Pharmacology (12.4)].

12.3 Pharmacokinetics

Pharmacokinetics in Adults: The pharmacokinetic properties of lamivudine have been studied in asymptomatic, HIV-1-infected adult patients after administration of single intravenous (IV) doses ranging from 0.25 to 8 mg/kg, as well as single and multiple (twice-daily regimen) oral doses ranging from 0.25 to 10 mg/kg.

The pharmacokinetic properties of lamivudine have also been studied as single and multiple oral doses ranging from 5 mg to 600 mg/day administered to HBV-infected patients.

The steady-state pharmacokinetic properties of the EPIVIR 300-mg tablet once daily for 7 days compared with the EPIVIR 150-mg tablet twice daily for 7 days were assessed in a crossover study in 60 healthy volunteers. EPIVIR 300 mg once daily resulted in lamivudine exposures that were similar to EPIVIR 150 mg twice daily with respect to plasma AUC24,ss; however, Cmax,ss was 66% higher and the trough value was 53% lower compared with the 150-mg twice-daily regimen. Intracellular lamivudine triphosphate exposures in peripheral blood mononuclear cells were also similar with respect to AUC24,ss and Cmax24,ss; however, trough values were lower compared with the 150-mg twice-daily regimen. Inter-subject variability was greater for intracellular lamivudine triphosphate concentrations versus lamivudine plasma trough concentrations. The clinical significance of observed differences for both plasma lamivudine concentrations and intracellular lamivudine triphosphate concentrations is not known.

Absorption and Bioavailability: Lamivudine was rapidly absorbed after oral administration in HIV-1-infected patients. Absolute bioavailability in 12 adult patients was 86% ± 16% (mean ± SD) for the 150-mg tablet and 87% ± 13% for the oral solution. After oral administration of 2 mg/kg twice a day to 9 adults with HIV-1, the peak serum lamivudine concentration (Cmax) was 1.5 ± 0.5 mcg/mL (mean ± SD). The area under the plasma concentration versus time curve (AUC) and Cmax increased in proportion to oral dose over the range from 0.25 to 10 mg/kg.

The accumulation ratio of lamivudine in HIV-1-positive asymptomatic adults with normal renal function was 1.50 following 15 days of oral administration of 2 mg/kg twice daily.

Effects of Food on Oral Absorption: An investigational 25-mg dosage form of lamivudine was administered orally to 12 asymptomatic, HIV-1-infected patients on 2 occasions, once in the fasted state and once with food (1,099 kcal; 75 grams fat, 34 grams protein, 72 grams carbohydrate). Absorption of lamivudine was slower in the fed state (Tmax: 3.2 ± 1.3 hours) compared with the fasted state (Tmax: 0.9 ± 0.3 hours); Cmax in the fed state was 40% ± 23% (mean ± SD) lower than in the fasted state. There was no significant difference in systemic exposure (AUC∞) in the fed and fasted states; therefore, EPIVIR Tablets and Oral Solution may be administered with or without food.

Distribution: The apparent volume of distribution after IV administration of lamivudine to 20 patients was 1.3 ± 0.4 L/kg, suggesting that lamivudine distributes into extravascular spaces. Volume of distribution was independent of dose and did not correlate with body weight.

Binding of lamivudine to human plasma proteins is low (<36%). In vitro studies showed that over the concentration range of 0.1 to 100 mcg/mL, the amount of lamivudine associated with erythrocytes ranged from 53% to 57% and was independent of concentration.

Metabolism: Metabolism of lamivudine is a minor route of elimination. In man, the only known metabolite of lamivudine is the trans-sulfoxide metabolite. Within 12 hours after a single oral dose of lamivudine in 6 HIV-1-infected adults, 5.2% ± 1.4% (mean ± SD) of the dose was excreted as the trans-sulfoxide metabolite in the urine. Serum concentrations of this metabolite have not been determined.

Elimination: The majority of lamivudine is eliminated unchanged in urine by active organic cationic secretion. In 9 healthy subjects given a single 300-mg oral dose of lamivudine, renal clearance was 199.7 ± 56.9 mL/min (mean ± SD). In 20 HIV-1-infected patients given a single IV dose, renal clearance was 280.4 ± 75.2 mL/min (mean ± SD), representing 71% ± 16% (mean ± SD) of total clearance of lamivudine.

In most single-dose studies in HIV-1-infected patients, HBV-infected patients, or healthy subjects with serum sampling for 24 hours after dosing, the observed mean elimination half-life (t½) ranged from 5 to 7 hours. In HIV-1-infected patients, total clearance was 398.5 ± 69.1 mL/min (mean ± SD). Oral clearance and elimination half-life were independent of dose and body weight over an oral dosing range of 0.25 to 10 mg/kg.

Special Populations: Renal Impairment: The pharmacokinetic properties of lamivudine have been determined in a small group of HIV-1-infected adults with impaired renal function (Table 7).

Table 7. Pharmacokinetic Parameters (Mean ± SD) After a Single 300-mg Oral Dose of Lamivudine in 3 Groups of Adults With Varying Degrees of Renal Function
Parameter | Creatinine Clearance Criterion; (Number of Subjects)
Parameter | >60 mL/min; (n = 6) | 10-30 mL/min; (n = 4) | <10 mL/min; (n = 6)
Creatinine clearance (mL/min) | 111 ± 14 | 28 ± 8 | 6 ± 2
Cmax (mcg/mL) | 2.6 ± 0.5 | 3.6 ± 0.8 | 5.8 ± 1.2
AUC∞ (mcg•hr/mL) | 11.0 ± 1.7 | 48.0 ± 19 | 157 ± 74
Cl/F (mL/min) | 464 ± 76 | 114 ± 34 | 36 ± 11

Exposure (AUC∞), Cmax, and half-life increased with diminishing renal function (as expressed by creatinine clearance). Apparent total oral clearance (Cl/F) of lamivudine decreased as creatinine clearance decreased. Tmax was not significantly affected by renal function. Based on these observations, it is recommended that the dosage of lamivudine be modified in patients with renal impairment [see Dosage and Administration (2.3)].

Based on a study in otherwise healthy subjects with impaired renal function, hemodialysis increased lamivudine clearance from a mean of 64 to 88 mL/min; however, the length of time of hemodialysis (4 hours) was insufficient to significantly alter mean lamivudine exposure after a single-dose administration. Continuous ambulatory peritoneal dialysis and automated peritoneal dialysis have negligible effects on lamivudine clearance. Therefore, it is recommended, following correction of dose for creatinine clearance, that no additional dose modification be made after routine hemodialysis or peritoneal dialysis.

It is not known whether lamivudine can be removed by continuous (24-hour) hemodialysis.

The effects of renal impairment on lamivudine pharmacokinetics in pediatric patients are not known.

Hepatic Impairment: The pharmacokinetic properties of lamivudine have been determined in adults with impaired hepatic function. Pharmacokinetic parameters were not altered by diminishing hepatic function; therefore, no dose adjustment for lamivudine is required for patients with impaired hepatic function. Safety and efficacy of lamivudine have not been established in the presence of decompensated liver disease.

Pediatric Patients: In Study NUCA2002, pharmacokinetic properties of lamivudine were assessed in a subset of 57 HIV-1-infected pediatric patients (age range: 4.8 months to 16 years, weight range: 5 to 66 kg) after oral and IV administration of 1, 2, 4, 8, 12, and 20 mg/kg/day. In the 9 infants and children (range: 5 months to 12 years of age) receiving oral solution 4 mg/kg twice daily (the usual recommended pediatric dose), absolute bioavailability was 66% ± 26% (mean ± SD), which was less than the 86% ± 16% (mean ± SD) observed in adults. The mechanism for the diminished absolute bioavailability of lamivudine in infants and children is unknown.

Systemic clearance decreased with increasing age in pediatric patients, as shown in Figure 1.

Figure 1. Systemic Clearance (L/hr•kg) of Lamivudine in Relation to Age

After oral administration of lamivudine 4 mg/kg twice daily to 11 pediatric patients ranging from 4 months to 14 years of age, Cmax was 1.1 ± 0.6 mcg/mL and half-life was 2.0 ± 0.6 hours. (In adults with similar blood sampling, the half-life was 3.7 ± 1 hours.) Total exposure to lamivudine, as reflected by mean AUC values, was comparable between pediatric patients receiving an 8-mg/kg/day dose and adults receiving a 4-mg/kg/day dose.

Distribution of lamivudine into cerebrospinal fluid (CSF) was assessed in 38 pediatric patients after multiple oral dosing with lamivudine. CSF samples were collected between 2 and 4 hours postdose. At the dose of 8 mg/kg/day, CSF lamivudine concentrations in 8 patients ranged from 5.6% to 30.9% (mean ± SD of 14.2% ± 7.9%) of the concentration in a simultaneous serum sample, with CSF lamivudine concentrations ranging from 0.04 to 0.3 mcg/mL.

Limited, uncontrolled pharmacokinetic and safety data are available from administration of lamivudine (and zidovudine) to 36 infants up to 1 week of age in 2 studies in South Africa. In these studies, lamivudine clearance was substantially reduced in 1-week-old neonates relative to pediatric patients (>3 months of age) studied previously. There is insufficient information to establish the time course of changes in clearance between the immediate neonatal period and the age-ranges >3 months old [see Adverse Reactions (6.1)].

Geriatric Patients: The pharmacokinetics of lamivudine after administration of EPIVIR to patients over 65 years of age have not been studied [see Use in Specific Populations (8.5)].

Gender: There are no significant gender differences in lamivudine pharmacokinetics.

Race: There are no significant racial differences in lamivudine pharmacokinetics.

Drug Interactions: Interferon Alfa: There was no significant pharmacokinetic interaction between lamivudine and interferon alfa in a study of 19 healthy male subjects [see Warnings and Precautions (5.4)].

Ribavirin: In vitro data indicate ribavirin reduces phosphorylation of lamivudine, stavudine, and zidovudine. However, no pharmacokinetic (e.g., plasma concentrations or intracellular triphosphorylated active metabolite concentrations) or pharmacodynamic (e.g., loss of HIV-1/HCV virologic suppression) interaction was observed when ribavirin and lamivudine (n = 18), stavudine (n = 10), or zidovudine (n = 6) were coadministered as part of a multi-drug regimen to HIV-1/HCV co-infected patients [see Warnings and Precautions (5.4)].

Trimethoprim/Sulfamethoxazole: Lamivudine and TMP/SMX were coadministered to 14 HIV-1-positive patients in a single-center, open-label, randomized, crossover study. Each patient received treatment with a single 300-mg dose of lamivudine and TMP 160 mg/SMX 800 mg once a day for 5 days with concomitant administration of lamivudine 300 mg with the fifth dose in a crossover design. Coadministration of TMP/SMX with lamivudine resulted in an increase of 43% ± 23% (mean ± SD) in lamivudine AUC∞, a decrease of 29% ± 13% in lamivudine oral clearance, and a decrease of 30% ± 36% in lamivudine renal clearance. The pharmacokinetic properties of TMP and SMX were not altered by coadministration with lamivudine [see Drug Interactions (7.3)].

Zidovudine: No clinically significant alterations in lamivudine or zidovudine pharmacokinetics were observed in 12 asymptomatic HIV-1-infected adult patients given a single dose of zidovudine (200 mg) in combination with multiple doses of lamivudine (300 mg q 12 hr) [see Drug Interactions (7.4)].

12.4 Microbiology

Mechanism of Action: Intracellularly, lamivudine is phosphorylated to its active 5′-triphosphate metabolite, lamivudine triphosphate (3TC-TP). The principal mode of action of 3TC-TP is the inhibition of HIV-1 reverse transcriptase (RT) via DNA chain termination after incorporation of the nucleotide analogue into viral DNA. 3TC-TP is a weak inhibitor of mammalian DNA polymerases α, β, and γ.

Antiviral Activity: The antiviral activity of lamivudine against HIV-1 was assessed in a number of cell lines (including monocytes and fresh human peripheral blood lymphocytes) using standard susceptibility assays. EC50 values (50% effective concentrations) were in the range of 0.003 to 15 µM (1 μM = 0.23 mcg/mL). HIV-1 from therapy-naive subjects with no amino acid substitutions associated with resistance gave median EC50 values of 0.429 µM (range: 0.200 to 2.007 µM) from Virco (n = 92 baseline samples from COLA40263) and 2.35 µM (1.37 to 3.68 µM) from Monogram Biosciences (n = 135 baseline samples from ESS30009). The EC50 values of lamivudine against different HIV-1 clades (A-G) ranged from 0.001 to 0.120 µM, and against HIV-2 isolates from 0.003 to 0.120 μM in peripheral blood mononuclear cells. Ribavirin (50 μM) decreased the anti-HIV-1 activity of lamivudine by 3.5 fold in MT-4 cells. In HIV-1-infected MT-4 cells, lamivudine in combination with zidovudine at various ratios exhibited synergistic antiretroviral activity. Please see the full prescribing information for EPIVIR-HBV for information regarding the inhibitory activity of lamivudine against HBV.

Resistance: Lamivudine-resistant variants of HIV-1 have been selected in cell culture. Genotypic analysis showed that the resistance was due to a specific amino acid substitution in the HIV-1 reverse transcriptase at codon 184 changing the methionine to either isoleucine or valine (M184V/I).

HIV-1 strains resistant to both lamivudine and zidovudine have been isolated from patients. Susceptibility of clinical isolates to lamivudine and zidovudine was monitored in controlled clinical trials. In patients receiving lamivudine monotherapy or combination therapy with lamivudine plus zidovudine, HIV-1 isolates from most patients became phenotypically and genotypically resistant to lamivudine within 12 weeks. In some patients harboring zidovudine-resistant virus at baseline, phenotypic sensitivity to zidovudine was restored by 12 weeks of treatment with lamivudine and zidovudine. Combination therapy with lamivudine plus zidovudine delayed the emergence of mutations conferring resistance to zidovudine.

Lamivudine-resistant HBV isolates develop substitutions (rtM204V/I) in the YMDD motif of the catalytic domain of the viral reverse transcriptase. rtM204V/I substitutions are frequently accompanied by other substitutions (rtV173L, rtL180M) which enhance the level of lamivudine resistance or act as compensatory mutations improving replication efficiency. Other substitutions detected in lamivudine-resistant HBV isolates include: rtL80I and rtA181T. Similar HBV mutants have been reported in HIV-1-infected patients who received lamivudine-containing antiretroviral regimens in the presence of concurrent infection with hepatitis B virus [see Warnings and Precautions (5.2)].

Cross-Resistance: Lamivudine-resistant HIV-1 mutants were cross-resistant to didanosine (ddI) and zalcitabine (ddC). In some patients treated with zidovudine plus didanosine or zalcitabine, isolates resistant to multiple reverse transcriptase inhibitors, including lamivudine, have emerged.

Genotypic and Phenotypic Analysis of On-Therapy HIV-1 Isolates From Patients With Virologic Failure: Study EPV20001: Fifty-three of 554 (10%) patients enrolled in EPV20001 were identified as virological failures (plasma HIV-1 RNA level ≥400 copies/mL) by Week 48. Twenty-eight patients were randomized to the lamivudine once-daily treatment group and 25 to the lamivudine twice-daily treatment group. The median baseline plasma HIV-1 RNA levels of patients in the lamivudine once-daily group and lamivudine twice-daily group were 4.9 log10 copies/mL and 4.6 log10 copies/mL, respectively.

Genotypic analysis of on-therapy isolates from 22 patients identified as virologic failures in the lamivudine once-daily group showed that isolates from 0/22 patients contained treatment-emergent amino acid substitutions associated with zidovudine resistance (M41L, D67N, K70R, L210W, T215Y/F, or K219Q/E), isolates from 10/22 patients contained treatment-emergent amino acid substitutions associated with efavirenz resistance (L100I, K101E, K103N, V108I, or Y181C), and isolates from 8/22 patients contained a treatment-emergent lamivudine resistance-associated substitution (M184I or M184V).

Genotypic analysis of on-therapy isolates from patients (n = 22) in the lamivudine twice-daily treatment group showed that isolates from 1/22 patients contained treatment-emergent zidovudine resistance substitutions, isolates from 7/22 contained treatment-emergent efavirenz resistance substitutions, and isolates from 5/22 contained treatment-emergent lamivudine resistance substitutions.

Phenotypic analysis of baseline-matched on-therapy HIV-1 isolates from patients (n = 13) receiving lamivudine once daily showed that isolates from 12/13 patients were susceptible to zidovudine; isolates from 8/13 patients exhibited a 25- to 295-fold decrease in susceptibility to efavirenz, and isolates from 7/13 patients showed an 85- to 299-fold decrease in susceptibility to lamivudine.

Phenotypic analysis of baseline-matched on-therapy HIV-1 isolates from patients (n = 13) receiving lamivudine twice daily showed that isolates from all 13 patients were susceptible to zidovudine; isolates from 3/13 patients exhibited a 21- to 342-fold decrease in susceptibility to efavirenz, and isolates from 4/13 patients exhibited a 29- to 159-fold decrease in susceptibility to lamivudine.

Study EPV40001: Fifty patients received zidovudine 300 mg twice daily plus abacavir 300 mg twice daily plus lamivudine 300 mg once daily and 50 patients received zidovudine 300 mg plus abacavir 300 mg plus lamivudine 150 mg all twice daily. The median baseline plasma HIV-1 RNA levels for patients in the 2 groups were 4.79 log10 copies/mL and 4.83 log10 copies/mL, respectively. Fourteen of 50 patients in the lamivudine once-daily treatment group and 9 of 50 patients in the lamivudine twice-daily group were identified as virologic failures.

Genotypic analysis of on-therapy HIV-1 isolates from patients (n = 9) in the lamivudine once-daily treatment group showed that isolates from 6 patients had an abacavir and/or lamivudine resistance-associated substitution M184V alone. On-therapy isolates from patients (n = 6) receiving lamivudine twice daily showed that isolates from 2 patients had M184V alone, and isolates from 2 patients harbored the M184V substitution in combination with zidovudine resistance-associated amino acid substitutions.

Phenotypic analysis of on-therapy isolates from patients (n = 6) receiving lamivudine once daily showed that HIV-1 isolates from 4 patients exhibited a 32- to 53-fold decrease in susceptibility to lamivudine. HIV-1 isolates from these 6 patients were susceptible to zidovudine.

Phenotypic analysis of on-therapy isolates from patients (n = 4) receiving lamivudine twice daily showed that HIV-1 isolates from 1 patient exhibited a 45-fold decrease in susceptibility to lamivudine and a 4.5-fold decrease in susceptibility to zidovudine.

13 NONCLINICAL TOXICOLOGY

13.1 Carcinogenesis, Mutagenesis, Impairment of Fertility

Long-term carcinogenicity studies with lamivudine in mice and rats showed no evidence of carcinogenic potential at exposures up to 10 times (mice) and 58 times (rats) those observed in humans at the recommended therapeutic dose for HIV-1 infection. Lamivudine was not active in a microbial mutagenicity screen or an in vitro cell transformation assay, but showed weak in vitro mutagenic activity in a cytogenetic assay using cultured human lymphocytes and in the mouse lymphoma assay. However, lamivudine showed no evidence of in vivo genotoxic activity in the rat at oral doses of up to 2,000 mg/kg, producing plasma levels of 35 to 45 times those in humans at the recommended dose for HIV-1 infection. In a study of reproductive performance, lamivudine administered to rats at doses up to 4,000 mg/kg/day, producing plasma levels 47 to 70 times those in humans, revealed no evidence of impaired fertility and no effect on the survival, growth, and development to weaning of the offspring.

13.2 Reproductive Toxicology Studies

Reproduction studies have been performed in rats and rabbits at orally administered doses up to 4,000 mg/kg/day and 1,000 mg/kg/day, respectively, producing plasma levels up to approximately 35 times that for the adult HIV dose. No evidence of teratogenicity due to lamivudine was observed. Evidence of early embryolethality was seen in the rabbit at exposure levels similar to those observed in humans, but there was no indication of this effect in the rat at exposure levels up to 35 times those in humans. Studies in pregnant rats and rabbits showed that lamivudine is transferred to the fetus through the placenta.

14 CLINICAL STUDIES

The use of EPIVIR is based on the results of clinical studies in HIV-1-infected patients in combination regimens with other antiretroviral agents. Information from trials with clinical endpoints or a combination of CD4+ cell counts and HIV-1 RNA measurements is included below as documentation of the contribution of lamivudine to a combination regimen in controlled trials.

14.1 Adults

Clinical Endpoint Study: NUCB3007 (CAESAR) was a multi-center, double-blind, placebo-controlled study comparing continued current therapy (zidovudine alone [62% of patients] or zidovudine with didanosine or zalcitabine [38% of patients]) to the addition of EPIVIR or EPIVIR plus an investigational non-nucleoside reverse transcriptase inhibitor (NNRTI), randomized 1:2:1. A total of 1,816 HIV-1-infected adults with 25 to 250 CD4+ cells/mm^3 (median = 122 cells/mm^3) at baseline were enrolled: median age was 36 years, 87% were male, 84% were nucleoside-experienced, and 16% were therapy-naive. The median duration on study was 12 months. Results are summarized in Table 8.

Table 8. Number of Patients (%) With at Least One HIV-1 Disease Progression Event or Death
Endpoint | Current Therapy; (n = 460) | EPIVIR plus; Current Therapy; (n = 896) | EPIVIR plus an; NNRTIa plus Current; Therapy; (n = 460)
HIV progression or death | 90 (19.6%) | 86 (9.6%) | 41 (8.9%)
Death | 27 (5.9%) | 23 (2.6%) | 14 (3.0%)
a An investigational non-nucleoside reverse transcriptase inhibitor not approved in the United States.

Surrogate Endpoint Studies: Dual Nucleoside Analogue Studies: Principal clinical trials in the initial development of lamivudine compared lamivudine/zidovudine combinations with zidovudine monotherapy or with zidovudine plus zalcitabine. These studies demonstrated the antiviral effect of lamivudine in a 2-drug combination. More recent uses of lamivudine in treatment of HIV-1 infection incorporate it into multiple-drug regimens containing at least 3 antiretroviral drugs for enhanced viral suppression.

Dose Regimen Comparison Surrogate Endpoint Studies in Therapy-Naive Adults: EPV20001 was a multi-center, double-blind, controlled study in which patients were randomized 1:1 to receive EPIVIR 300 mg once daily or EPIVIR 150 mg twice daily, in combination with zidovudine 300 mg twice daily and efavirenz 600 mg once daily. A total of 554 antiretroviral treatment-naive HIV-1-infected adults enrolled: male (79%), Caucasian (50%), median age of 35 years, baseline CD4+ cell counts of 69 to 1,089 cells/mm^3 (median = 362 cells/mm^3), and median baseline plasma HIV-1 RNA of 4.66 log10 copies/mL. Outcomes of treatment through 48 weeks are summarized in Figure 2 and Table 9.

Figure 2. Virologic Response Through Week 48, EPV20001ab(Intent-to-Treat)

a Roche AMPLICOR HIV-1 MONITOR.

bResponders at each visit are patients who had achieved and maintained HIV-1 RNA <400 copies/mL without discontinuation by that visit.

Table 9. Outcomes of Randomized Treatment Through 48 Weeks (Intent-to-Treat)
Outcome | EPIVIR 300 mg; Once Daily; plus RETROVIR; plus Efavirenz; (n = 278) | EPIVIR 150 mg; Twice Daily; plus RETROVIR; plus Efavirenz; (n = 276)
Respondera | 67% | 65%
Virologic failureb | 8% | 8%
Discontinued due to clinical progression | <1% | 0%
Discontinued due to adverse events | 6% | 12%
Discontinued due to other reasonsc | 18% | 14%
a Achieved confirmed plasma HIV-1 RNA <400 copies/mL and maintained through 48 weeks.
b Achieved suppression but rebounded by Week 48, discontinued due to virologic failure, insufficient viral response according to the investigator, or never suppressed through Week 48.
c Includes consent withdrawn, lost to followup, protocol violation, data outside the study-defined schedule, and randomized but never initiated treatment.

The proportions of patients with HIV-1 RNA <50 copies/mL (via Roche Ultrasensitive assay) through Week 48 were 61% for patients receiving EPIVIR 300 mg once daily and 63% for patients receiving EPIVIR 150 mg twice daily. Median increases in CD4+ cell counts were 144 cells/mm^3 at Week 48 in patients receiving EPIVIR 300 mg once daily and 146 cells/mm^3 for patients receiving EPIVIR 150 mg twice daily.

A small, randomized, open-label pilot study, EPV40001, was conducted in Thailand. A total of 159 treatment-naive adult patients (male 32%, Asian 100%, median age 30 years, baseline median CD4+ cell count 380 cells/mm^3, median plasma HIV-1 RNA 4.8 log10 copies/mL) were enrolled. Two of the treatment arms in this study provided a comparison between lamivudine 300 mg once daily (n = 54) and lamivudine 150 mg twice daily (n = 52), each in combination with zidovudine 300 mg twice daily and abacavir 300 mg twice daily. In intent-to-treat analyses of 48-week data, the proportions of patients with HIV-1 RNA below 400 copies/mL were 61% (33/54) in the group randomized to once-daily lamivudine and 75% (39/52) in the group randomized to receive all 3 drugs twice daily; the proportions with HIV-1 RNA below 50 copies/mL were 54% (29/54) in the once-daily lamivudine group and 67% (35/52) in the all-twice-daily group; and the median increases in CD4+ cell counts were 166 cells/mm^3 in the once-daily lamivudine group and 216 cells/mm^3 in the all-twice-daily group.

14.2 Pediatric Patients

Clinical Endpoint Study: ACTG300 was a multi-center, randomized, double-blind study that provided for comparison of EPIVIR plus RETROVIR (zidovudine) with didanosine monotherapy. A total of 471 symptomatic, HIV-1-infected therapy-naive (≤56 days of antiretroviral therapy) pediatric patients were enrolled in these 2 treatment arms. The median age was 2.7 years (range: 6 weeks to 14 years), 58% were female, and 86% were non-Caucasian. The mean baseline CD4+ cell count was 868 cells/mm^3 (mean: 1,060 cells/mm^3 and range: 0 to 4,650 cells/mm^3 for patients ≤5 years of age; mean: 419 cells/mm^3 and range: 0 to 1,555 cells/mm^3 for patients >5 years of age) and the mean baseline plasma HIV-1 RNA was 5.0 log10 copies/mL. The median duration on study was 10.1 months for the patients receiving EPIVIR plus RETROVIR and 9.2 months for patients receiving didanosine monotherapy. Results are summarized in Table 10.

Table 10. Number of Patients (%) Reaching a Primary Clinical Endpoint (Disease Progression or Death)
Endpoint | EPIVIR plus RETROVIR; (n = 236) | Didanosine; (n = 235)
HIV disease progression or death (total) | 15 (6.4%) | 37 (15.7%)
Physical growth failure | 7 (3.0%) | 6 (2.6%)
Central nervous system deterioration | 4 (1.7%) | 12 (5.1%)
CDC Clinical Category C | 2 (0.8%) | 8 (3.4%)
Death | 2 (0.8%) | 11 (4.7%)

16 HOW SUPPLIED/STORAGE AND HANDLING

EPIVIR Scored Tablets, 150 mg

White, diamond-shaped, scored, film-coated tablets debossed with “GX CJ7” on both sides.

Bottle of 6 tablets (NDC 21695-367-06) with child-resistant closure.

Recommended Storage:

Store in tightly closed bottles at 25°C (77°F) [see USP Controlled Room Temperature].

17 PATIENT COUNSELING INFORMATION

17.1 Advice for the Patient

Information About Therapy With EPIVIR: EPIVIR is not a cure for HIV-1 infection and patients may continue to experience illnesses associated with HIV-1 infection, including opportunistic infections. Patients should remain under the care of a physician when using EPIVIR. Patients should be advised that the use of EPIVIR has not been shown to reduce the risk of transmission of HIV-1 to others through sexual contact or blood contamination.

Patients should be advised that the long-term effects of EPIVIR are unknown at this time.

Patients should be advised of the importance of taking EPIVIR with combination therapy on a regular dosing schedule and to avoid missing doses.

EPIVIR should not be coadministered with drugs containing lamivudine or emtricitabine, including COMBIVIR (lamivudine/zidovudine) Tablets, EPZICOM (abacavir sulfate and lamivudine) Tablets, TRIZIVIR (abacavir sulfate, lamivudine, and zidovudine), ATRIPLA (efavirenz, emtricitabine, and tenofovir), EMTRIVA (emtricitabine) or TRUVADA (emtricitabine and tenofovir) [see Warnings and Precautions (5.3)].

Redistribution/Accumulation of Body Fat: Patients should be informed that redistribution or accumulation of body fat may occur in patients receiving antiretroviral therapy, including EPIVIR, and that the cause and long-term health effects of these conditions are not known at this time [see Warnings and Precautions (5.7)].

Differences in Formulations of EPIVIR: Patients should be advised that EPIVIR Tablets and Oral Solution contain a higher dose of the same active ingredient (lamivudine) as EPIVIR-HBV Tablets and Oral Solution. If a decision is made to include lamivudine in the HIV-1 treatment regimen of a patient co-infected with HIV-1 and HBV, the formulation and dosage of lamivudine in EPIVIR (not EPIVIR-HBV) should be used [see Warnings and Precautions (5.2)].

Co-infection With HIV-1 and HBV: Patients co-infected with HIV-1 and HBV should be informed that deterioration of liver disease has occurred in some cases when treatment with lamivudine was discontinued. Patients should be advised to discuss any changes in regimen with their physician [see Warnings and Precautions (5.2)].

Risk of Pancreatitis: Parents or guardians should be advised to monitor pediatric patients for signs and symptoms of pancreatitis [see Warnings and Precautions (5.5)].

Sucrose Content of EPIVIR Oral Solution: Diabetic patients should be advised that each 15-mL dose of EPIVIR Oral Solution contains 3 grams of sucrose [see Description (11)].

COMBIVIR, EPIVIR, EPIVIR-HBV, EPZICOM, and TRIZIVIR are registered trademarks of GlaxoSmithKline. ATRIPLA, EMTRIVA, and TRUVADA are trademarks of their respective owners and are not trademarks of GlaxoSmithKline. The makers of these brands are not affiliated with and do not endorse GlaxoSmithKline or its products.

GlaxoSmithKline
Research Triangle Park, NC 27709

Manufactured under agreement from
Shire Pharmaceuticals Group plc
Basingstoke, UK

©2009, GlaxoSmithKline. All rights reserved.

Repackaged by:

Rebel Distributors Corp

Thousand Oaks, CA 91320

PACKAGE LABEL

PRINCIPAL DISPLAY PANEL

NDC 21695-367-06

EPIVIR®

(lamivudine)

TABLETS

150 mg

Rx only

6 Tablets

Each scored tablet contains 150 mg of lamivudine.

See prescribing information for Dosage and Administration.

Store at 25oC (77oF); excursions permitted to 15o to 30oC (59o to 86oF) [see USP Controlled Room Temperature].

Manufactured under agreement from Shire Pharmaceuticals Group plc

Basingstoke, UK

GlaxoSmithKline

Research Triangle Park, NC 27709

Made in Singapore

A056094 Rev.5/08

Repackaged by:

Rebel Distributors Corp

Thousand Oaks, CA 91320